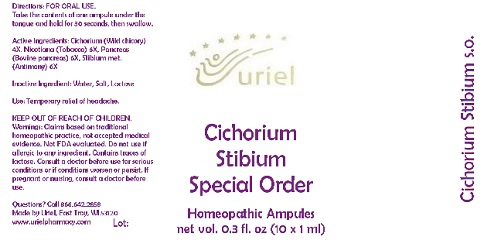 DRUG LABEL: Cichorium Stibium Special Order
NDC: 48951-3093 | Form: LIQUID
Manufacturer: Uriel Pharmacy Inc.
Category: homeopathic | Type: HUMAN OTC DRUG LABEL
Date: 20180516

ACTIVE INGREDIENTS: CICHORIUM INTYBUS WHOLE 4 [hp_X]/1 mL; TOBACCO LEAF 6 [hp_X]/1 mL; SUS SCROFA PANCREAS 6 [hp_X]/1 mL; ANTIMONY 6 [hp_X]/1 mL
INACTIVE INGREDIENTS: WATER; SODIUM CHLORIDE

Cichorium Stibium Special Order

INDICATIONS AND USAGE

Directions: FOR ORAL USE.

DOSAGE AND ADMINISTRATION

Take the contents of one ampule under the tongue and hold for 30 seconds, then swallow.

ACTIVE INGREDIENT

Active Ingredients: Cichorium (Wild chicory) 4X, Nicotiana (Tobacco) 6X, Pancreas (Bovine pancreas) 6X, Stibium met. (Antimony) 6X

Inactive Ingredient: Water, Salt

PURPOSE

Use: Temporary relief of headache.

KEEP OUT OF REACH OF CHILDREN.

WARNINGS

Warnings: Claims based on traditional homeopathic practice, not accepted medical evidence. Not FDA evaluated. Do not use if allergic to any ingredient. Contains traces of lactose. Consult a doctor before use for serious conditions or if conditions worsen or persist. If pregnant or nursing, consult a doctor before use.

QUESTIONS

Questions? Call 866.642.2858 Made by Uriel, East Troy, WI 53120 www.urielpharmacy.com